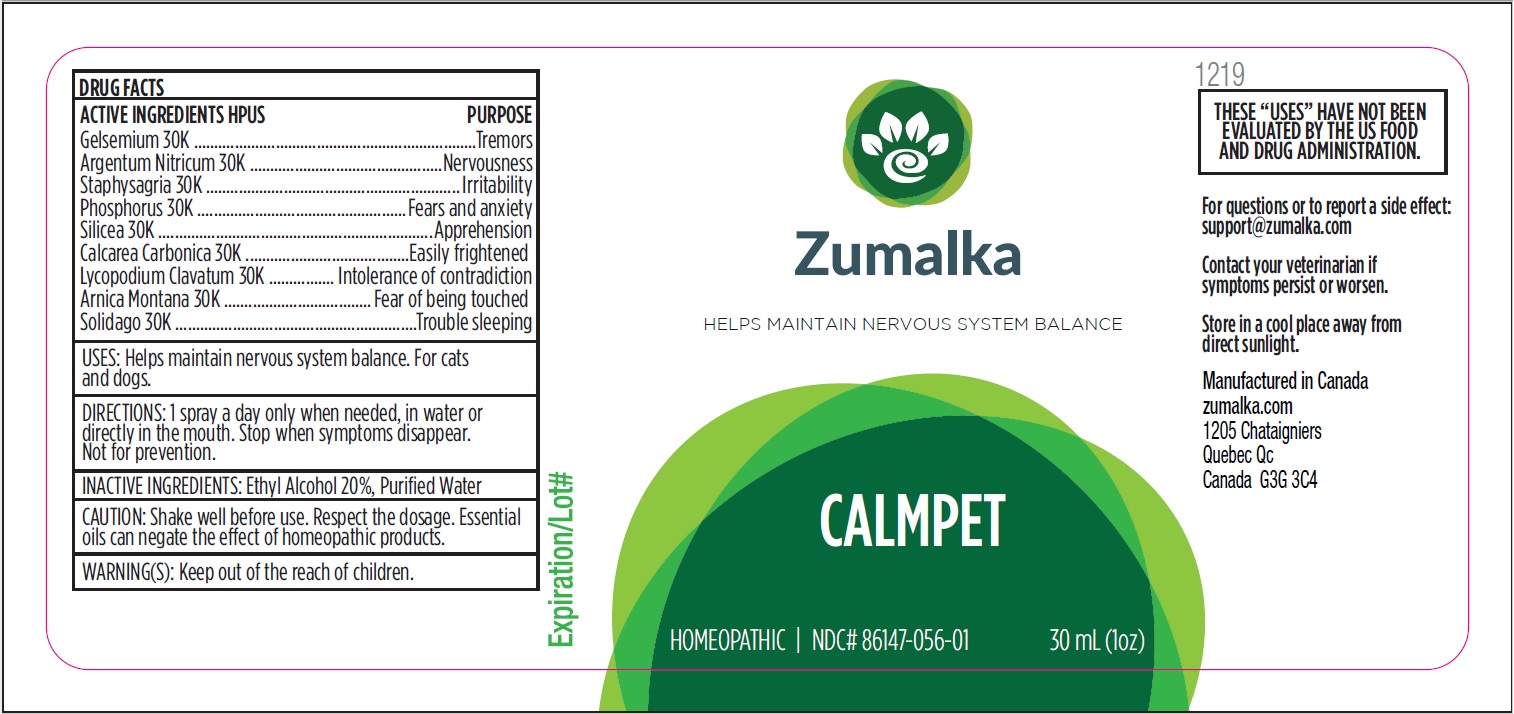 DRUG LABEL: CALMPET
NDC: 86147-056 | Form: LIQUID
Manufacturer: Groupe Cyrenne Inc.
Category: homeopathic | Type: OTC ANIMAL DRUG LABEL
Date: 20251120

ACTIVE INGREDIENTS: GELSEMIUM SEMPERVIRENS ROOT 30 [kp_C]/30 mL; SILVER NITRATE 30 [kp_C]/30 mL; PHOSPHORUS 30 [kp_C]/30 mL; OYSTER SHELL CALCIUM CARBONATE, CRUDE 30 [kp_C]/30 mL; LYCOPODIUM CLAVATUM SPORE 30 [kp_C]/30 mL; ARNICA MONTANA FLOWER 30 [kp_C]/30 mL; DELPHINIUM STAPHISAGRIA SEED 30 [kp_C]/30 mL; SILICON DIOXIDE 30 [kp_C]/30 mL; SOLIDAGO VIRGAUREA FLOWERING TOP 30 [kp_C]/30 mL
INACTIVE INGREDIENTS: ALCOHOL; WATER

Active ingredients Purpose

Gelsemium 30k Tremors

Argentum Nitricum 30k Nervousness

Phosphorus 30k Fears and anxiety

Calcarea Carbonica 30k Easily frightened

Lycopodium Clavatum 30k Intolerance of contradiction

Arnica Montana 30k Fear of being touched

Staphysagria 30k Irritability

Silicea 30k Apprehension

Solidago 30k Trouble sleeping

Uses

Helps maintain nervous system balance. For cats and dogs.

Warnings

Keep out of reach of children.

Direction

1 spray a day only when needed, in water or directly in the mouth. Stop when symptoms disappear. Not for prevention.

Inactive ingredients

Ethyl alcohol 20%, purified water